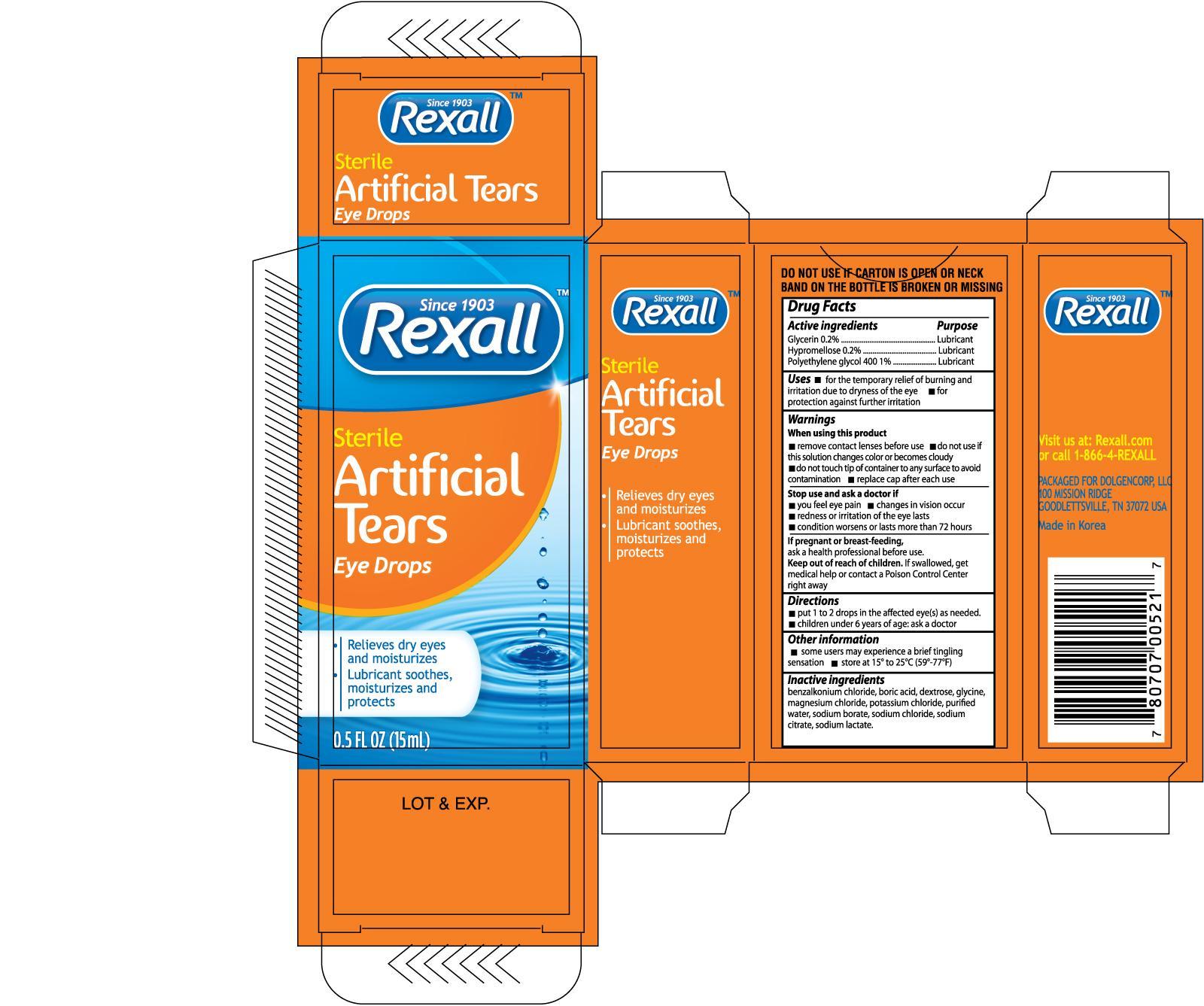 DRUG LABEL: Rexall Sterile Artificial Tears Eye Drops
NDC: 55910-522 | Form: SOLUTION
Manufacturer: Dolgencorp Inc
Category: otc | Type: HUMAN OTC DRUG LABEL
Date: 20130630

ACTIVE INGREDIENTS: GLYCERIN 0.002 mg/1 mg; HYPROMELLOSES 0.002 mg/1 mg; POLYETHYLENE GLYCOL 400 0.01 mg/1 mg
INACTIVE INGREDIENTS: BENZALKONIUM CHLORIDE; BORIC ACID; DEXTROSE; GLYCINE; MAGNESIUM CHLORIDE; POTASSIUM CHLORIDE; WATER; SODIUM BORATE; SODIUM CHLORIDE; SODIUM CITRATE; SODIUM LACTATE

Drug Facts

Active ingredients Purpose

Glycerin 0.2%..................................................................................Lubricant

Hypromellose 0.2%..........................................................................Lubricant

Polyethylene glycol 400 1%..............................................................Lubricant

Uses

- for the temporary relief of burning and irritation due to dryness of the eye
- for protection against further irritation

Warnings for external use only

When using this product

- remove contact lenses before use
- do not use if this solution changes color or becomes cloudy
- do not touch tip of container or any surface to avoid contamination
- replace cap after each use

Stop use and ask a doctor if

- you feel eye pain
- changes in vision occur
- redness or irritation of the eye lasts
- condition worsens or last more than 72 hours

PREGNANCY OR BREAST FEEDING

If pregnant or breast-feeding, ask a health professional before use.

Keep out of reach of children. If swallowed, get medical help or contact a Poison Control Center right away

Directions

- put 1 to 2 drops in the affected eye(s) as needed.
- children under 6 years of age: ask a doctor.

Other information

- some users may experience a brief tingling sensation
- store at 15° to 25°C (59°-77°F)

INACTIVE INGREDIENT

Inactive ingredients benzalkonium chloride, boric acid, dextrose, glycine, magnesium chloride, potassium chloride, purified water, sodium borate, sodium chloride, sodium citrate, sodium lactate.

DOSAGE AND ADMINISTRATION

Packaged For:

Dolgencorp, LLC

100 Mission Ridge

Goodlettsville, TN 37072 USA

Made in Korea